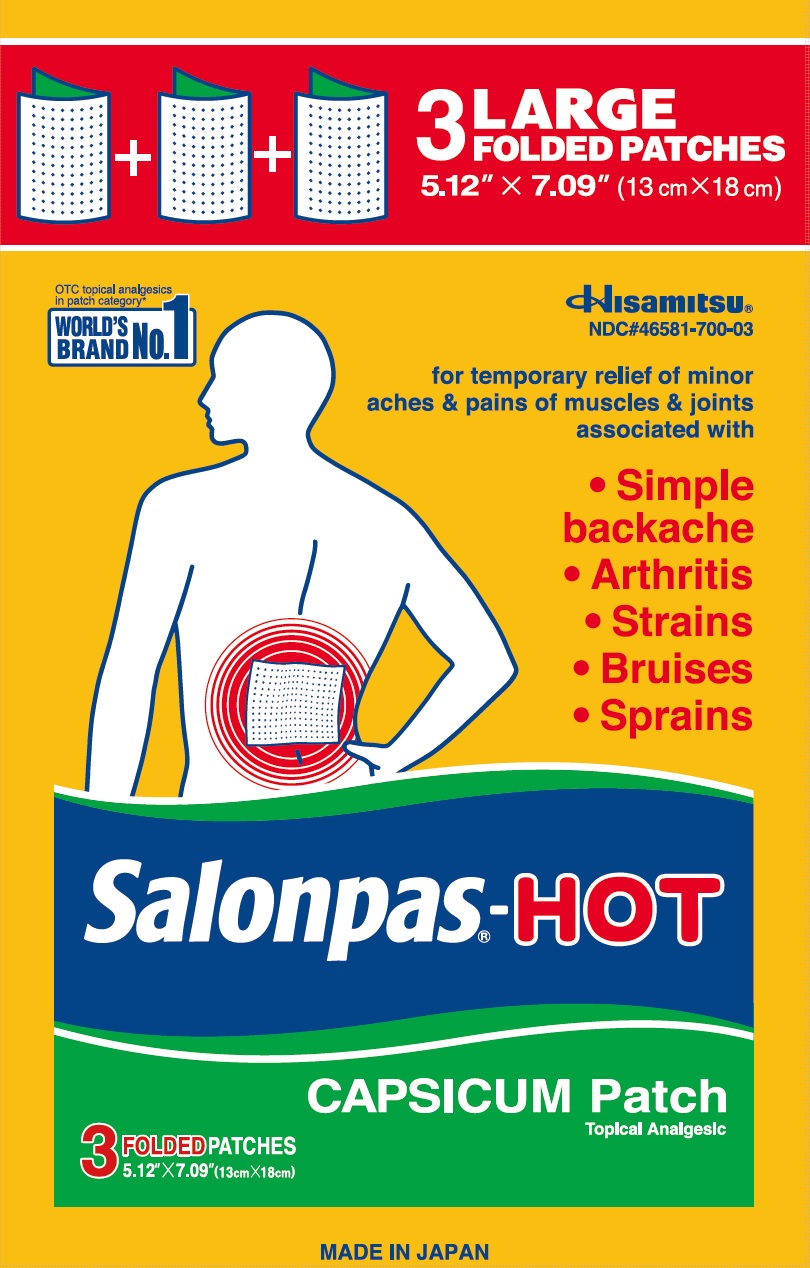 DRUG LABEL: SALONPAS-HOT CAPSICUM
NDC: 46581-700 | Form: PATCH
Manufacturer: Hisamitsu Pharmaceutical Co., Inc.
Category: otc | Type: HUMAN OTC DRUG LABEL
Date: 20251215

ACTIVE INGREDIENTS: CAPSICUM 0.025 g/100 g
INACTIVE INGREDIENTS: BUTYLATED HYDROXYTOLUENE; NATURAL LATEX RUBBER; SILICON DIOXIDE; TITANIUM DIOXIDE; ZINC OXIDE

Active ingredient

Capsicum extract 0.025% as Capsaicin

Purpose

Topical analgesic

Uses

For temporary relief of minor aches and pains of muscles and joints associated with:

- simple backache
- arthritis
- strains
- bruises
- sprains

Warnings

For external use only

Do not use

- on wounds or damaged skin
- with a heating pad
- if you are allergic to any ingredients of this product

When using this product

- use only as directed
- avoid contact with the eyes, mucous membranes or rashes
- do not bandage tightly
- discontinue use at least 1 hour before a bath or shower
- do not use immediately after a bath or shower

Stop use and ask a doctor if

- rash, itching or excessive skin irritation develops
- conditions worsen
- symptoms persist for more than 7 days
- symptoms clear up and occur again within a few days

If pregnant or breast-feeding,

ask a health professional before use.

Keep out of reach of children.

If swallowed, get medical help or contact a Poison Control Center right away.

Directions

Adults and children 12 years of age and over:

- clean and dry affected area
- remove patch from film
- apply to affected area not more than 3 to 4 times daily
- remove patch from the skin after at most 8 hours' application

Children under 12 years of age: consult a doctor

Other information

- Avoid storing product in direct sunlight
- Protect product from excessive moisture

Inactive ingredients

butylated hydroxytoluene, hydrogenated rosin glycerol ester, maleated rosin glycerin ester, natural rubber latex, polybutene, polyisobutylene, silicon dioxide, titanium dioxide, zinc oxide

Questions or comments?

Toll free 1-800-826-8861 www.salonpas.us

Principal Display Panel

3 LARGE FOLDED PATCHES
5.12" X 7.09"(13 cm X 18 cm)
OTC topical analgesics in patch category*
WORLD'S BRAND NO.1
Hisamitsu
NDC#46581-700-03
for temporary relief of minor aches and pains of muscles and joints associated with
Simple backache
Arthritis
Strains
Bruises
Sprains
Salonpas-HOT
CAPSICUM Patch
Topical Analgesic
3 FOLDED PATCHES
5.12" X 7.09" (13cm X 18cm)
MADE IN JAPAN